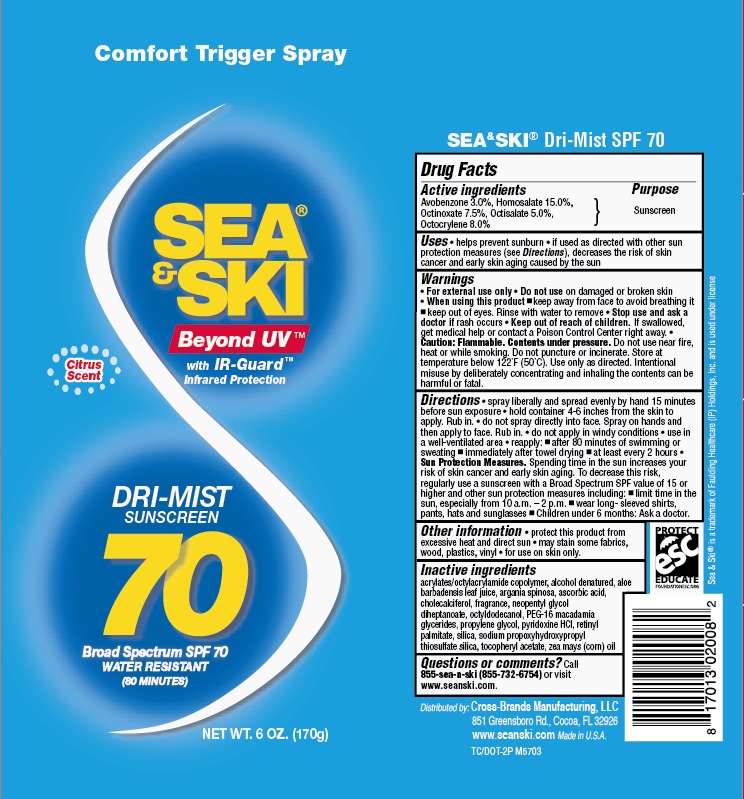 DRUG LABEL: General Protection
NDC: 71153-2008 | Form: AEROSOL, SPRAY
Manufacturer: Cross-Brands Manufacturing LLC
Category: otc | Type: HUMAN OTC DRUG LABEL
Date: 20190108

ACTIVE INGREDIENTS: AVOBENZONE 3 g/1 g; OCTISALATE 5 g/1 g; OCTINOXATE 7.5 g/1 g; OCTOCRYLENE 8 g/1 g; HOMOSALATE 15 g/1 g
INACTIVE INGREDIENTS: ALOE VERA LEAF 0.1 g/1 g

Sea & Ski SPF 70 CSpray